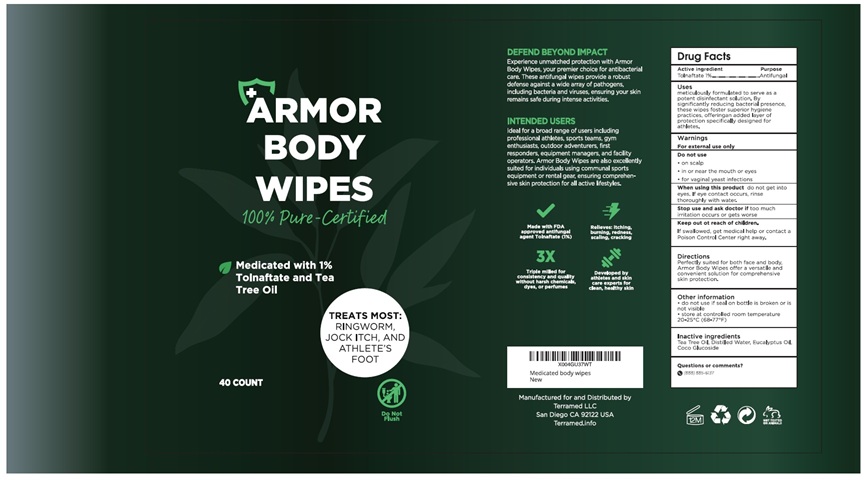 DRUG LABEL: Terramed Just Think Comfort Antifungal Medicated Body Wipes
NDC: 83004-018 | Form: CLOTH
Manufacturer: Rida LLC
Category: otc | Type: HUMAN OTC DRUG LABEL
Date: 20250306

ACTIVE INGREDIENTS: TOLNAFTATE 10 g/1000 mL
INACTIVE INGREDIENTS: TEA TREE OIL; WATER; EUCALYPTUS OIL; COCO-GLUCOSIDE

Active Ingredient

Tolnaftate 1%

Purpose

Antifungal foot wipes

Uses

meticulously formulated to serve as a potent disinfectant solution. By significantly reducing bacterial presence, these wipes foster superior hygiene practices. offeringan added layer of protection specifically designed for athletes.

Warnings

For External use only
Do not use on

- on scalp
- in or near the mouth or eyes
- or vaginal yeast infections

When using this productdo not get into eyes. If eye contact occurs, rinse thoroughly with water.

Stop use and ask doctor iftoo much irritation occurs or gets worse

Keep out of reach of childrenIf swallowed, get medical help or contact a Poison Control Center right away.

Directions

Perfectly suited for both face and body, Armor body wipes offer a versatile and convenient solution for comprehensive skin protection.

Other information

do not use if seal on bottle is broken or is not visible

store at controlled room temperature 20-25°C (68-77° F)

Inactive ingredients

Tea Tree Oil, Distilled Water , Eucalyptus Oil, Coco Glucoside